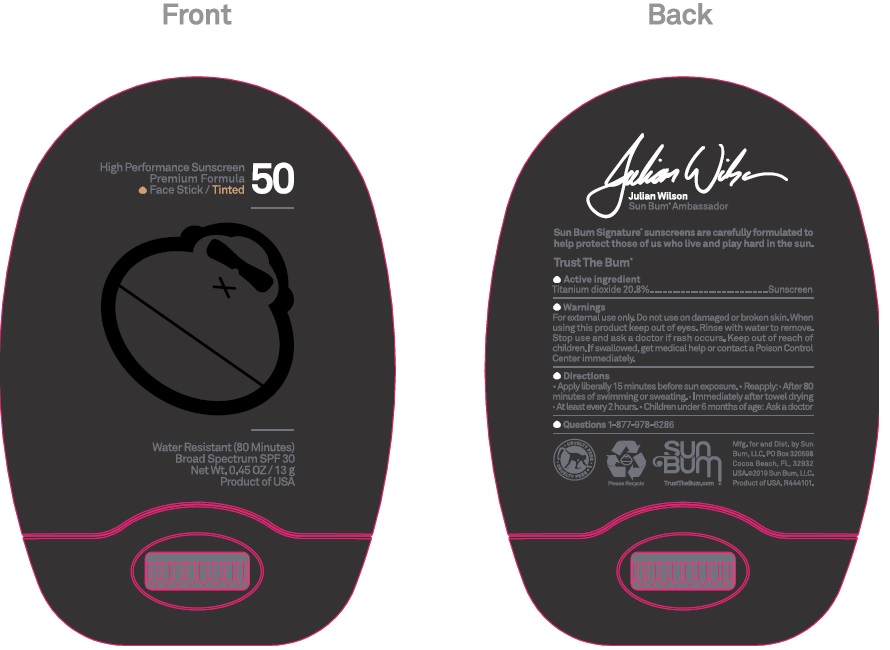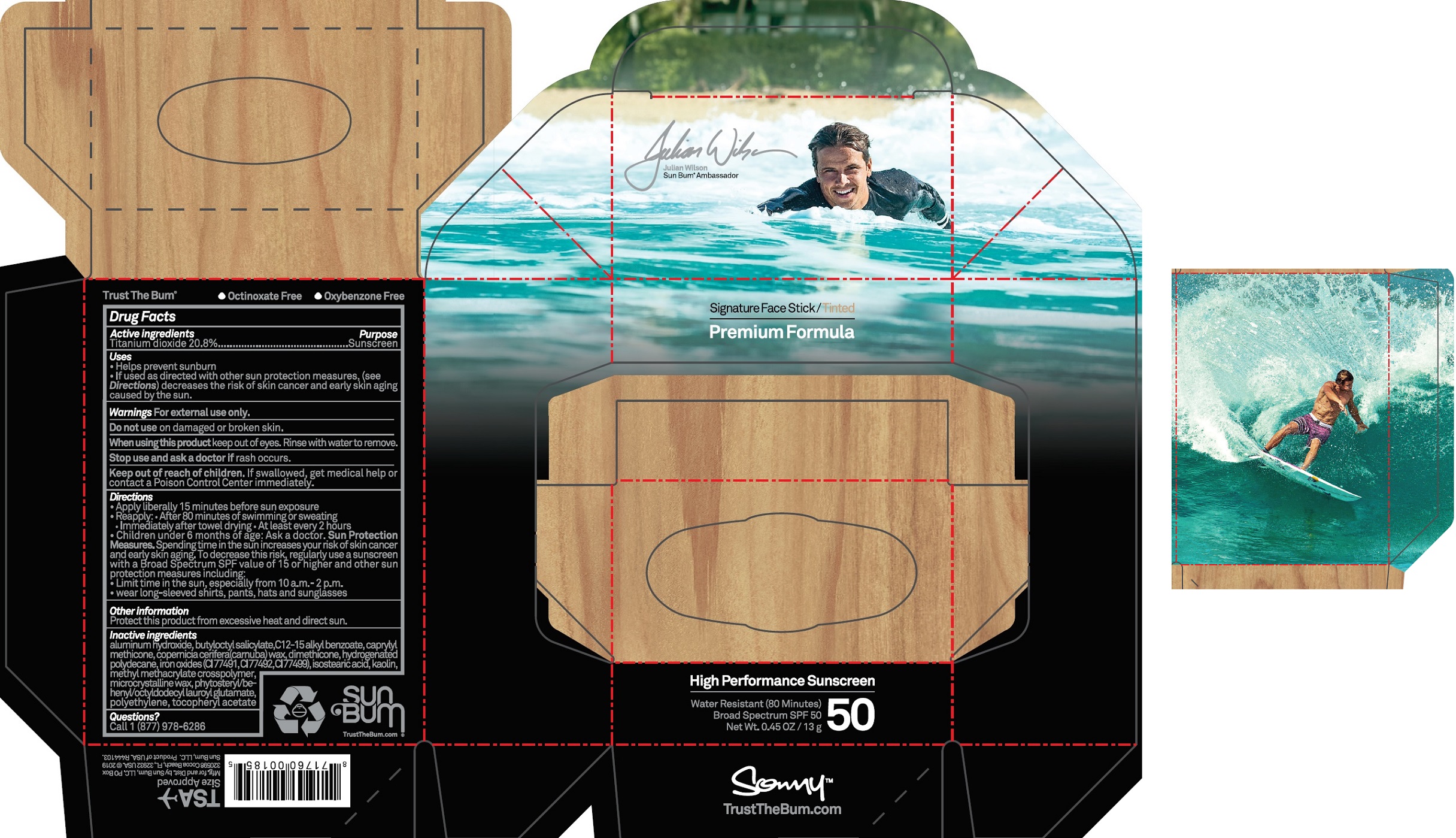 DRUG LABEL: Signature SPF 50 Tinted Face
NDC: 69039-609 | Form: STICK
Manufacturer: Sun Bum LLC
Category: otc | Type: HUMAN OTC DRUG LABEL
Date: 20220322

ACTIVE INGREDIENTS: TITANIUM DIOXIDE 208 mg/1 g
INACTIVE INGREDIENTS: ALUMINUM HYDROXIDE; BUTYLOCTYL SALICYLATE; ALKYL (C12-15) BENZOATE; CAPRYLYL TRISILOXANE; CARNAUBA WAX; DIMETHICONE; FERRIC OXIDE RED; FERRIC OXIDE YELLOW; FERROSOFERRIC OXIDE; ISOSTEARIC ACID; KAOLIN; METHYL METHACRYLATE/GLYCOL DIMETHACRYLATE CROSSPOLYMER; MICROCRYSTALLINE WAX; HIGH DENSITY POLYETHYLENE; .ALPHA.-TOCOPHEROL ACETATE

Signature SPF 50 Tinted Face Stick

Active ingredients

Titanium dioxide 20.8%

Purpose

Sunscreen

Uses

- Helps prevent sunburn
- If used as directed with other sun protection measures, (see Directions) decreases the risk of skin cancer and early skin aging caused by the sun

Warnings

For external use only

Do not use

on damaged or broken skin.

When using this product

keep out of eyes. Rinse with water to remove.

Stop use and ask a doctor

if rash occurs

Keep out of reach of children.

If swallowed, get medical help or contact a Poison Control Center immediately.

Directions

- Apply liberally 15 minutes before sun exposure
- Reapply: After 80 minutes of swimming or sweating
- Immediately after towel drying
- At least every 2 hours
- Children under 6 months of age: Ask a doctor

Sun Protection Measures. Spending time in the sun increases your risk of skin cancer and early skin aging. To decrease this risk, regularly use a sunscreen with a Broad Spectrum SPF value of 15 or higher and other sun protection measures including:

- Limit time in the sun, especially from 10 a.m.-2 p.m.
- Wear long-sleeved shirts, pants, hats and sunglasses

Other information

protect this product from excessive heat and direct sun

Inactive ingredients

aluminum hydroxide, butyloctyl salicylate, C12-15 alkyl benzoate, caprylyl methicone, copernicia cerifera (carnauba) wax, dimethicone, hydrogenated polydecane, iron oxides (CI 77491 CI 77492, CI 77499), isostearic acid, kaolin, methyl methacrylate crosspolymer, microcrystalline wax, phytosteryl/behynyl/octyldodecyl lauroyl glutamate, polyethylene, tocopheryl acetate

Questions?

1 (877) 978-6286